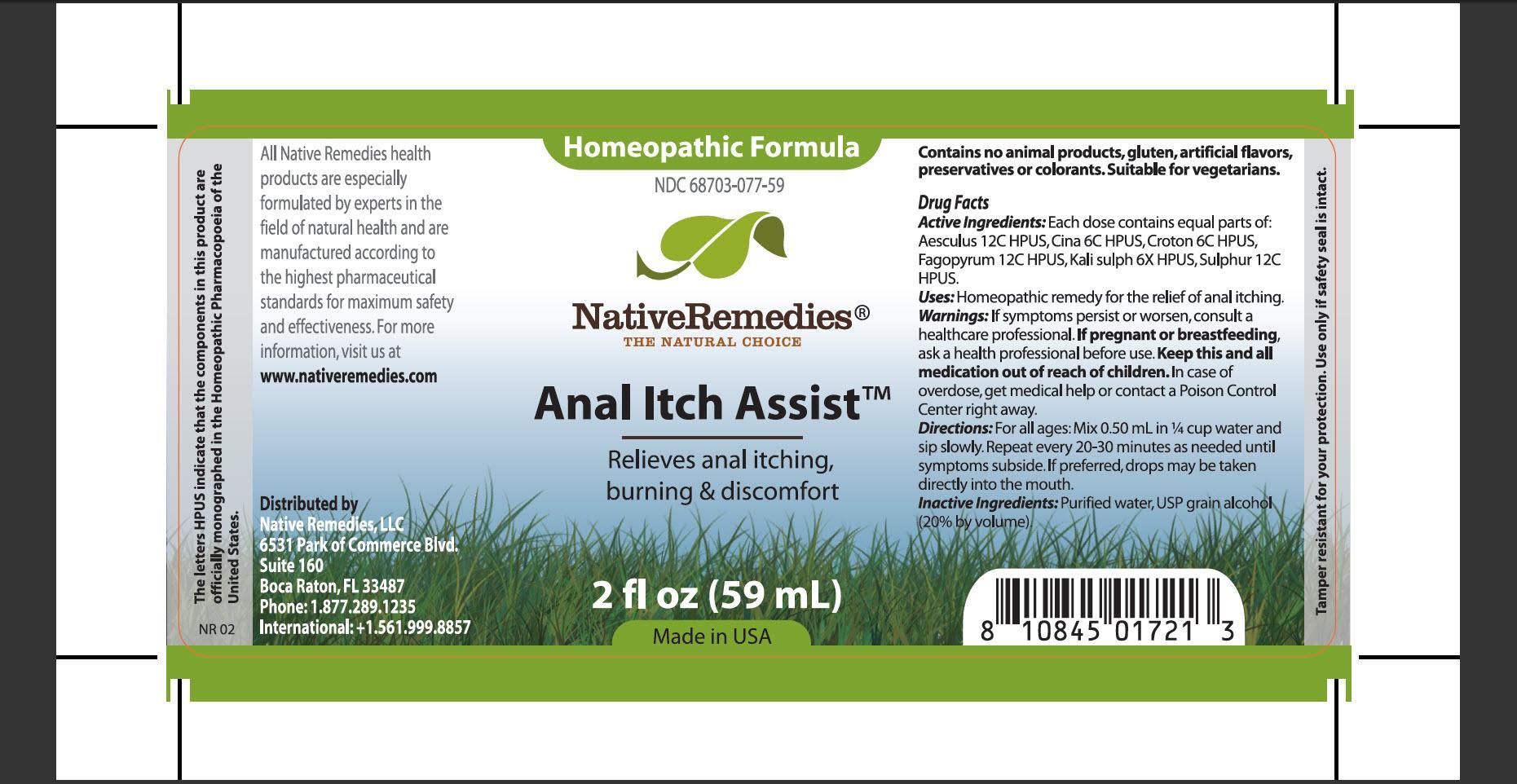 DRUG LABEL: Anal Itch Assist
NDC: 68703-077 | Form: TINCTURE
Manufacturer: Native Remedies, LLC
Category: homeopathic | Type: HUMAN OTC DRUG LABEL
Date: 20131021

ACTIVE INGREDIENTS: HORSE CHESTNUT 12 [hp_C]/59 mL; ARTEMISIA CINA PRE-FLOWERING TOP 6 [hp_C]/59 mL; CROTON TIGLIUM SEED 6 [hp_C]/59 mL; FAGOPYRUM ESCULENTUM 12 [hp_C]/59 mL; POTASSIUM SULFATE 6 [hp_X]/59 mL; SULFUR 12 [hp_C]/59 mL
INACTIVE INGREDIENTS: WATER; ALCOHOL

Anal Itch Assit

PURPOSE

Relieves anal itching, burning and discomfort

Drug Facts
Active Ingredients: Each dose contains equal parts of: Aesculus 12C HPUS, Cina 6C HPUS, Croton 6C HPUS, Fagopyrum 12C HPUS, Kali sulph 6X HPUS, Sulphur 12C HPUS

INDICATIONS AND USAGE

Uses: Homeopathic remedy for the relief of anal itching

WARNINGS

Warnings: If symptoms persist or worsen, consult a healthcare professional

PREGNANCY OR BREAST FEEDING

If pregnant or breastfeeding, ask a health professional

KEEP OUT OF REACH OF CHILDREN

Keep this and all medication out of reach of children

OVERDOSAGE

In case of overdose, get medical help or contact a Poison Control Center right away

DOSAGE AND ADMINISTRATION

Directions:For all ages: Mix 0.50 mL in 1/4 cup water and sip slowly. Repeat every 20-30 minutes as needed until symptoms subside. If preferred, drops may be taken directly into the mouth

INACTIVE INGREDIENT

Inactive Ingredients: Purified water, USP grain alcohol (20% by volume)

PATIENT COUNSELING INFORMATION

The letters HPUS indicate that the components in this product are officially monographed in the Homeopathic Pharmacopoeia of the United States

All Native Remedies health products are especially formulated by experts in the field of natural health and are manufactured according to the highest pharmaceutical standards for maximum safety and effectiveness. For more information visit us at www.nativeremedies.com

Distributed by
Native Remedies, LLC
6531 Park of Commerce Blvd.
Suite 160
Boca Raton, FL 33487
Phone: 1.877.289.1235
International: +1.561.999.8857

Contains no animal products, gluten, artificial flavors, preservatives or colorants. Suitable for vegetarians

STORAGE AND HANDLING

Tamper resistant for your protection. Use only if safety seal is intact